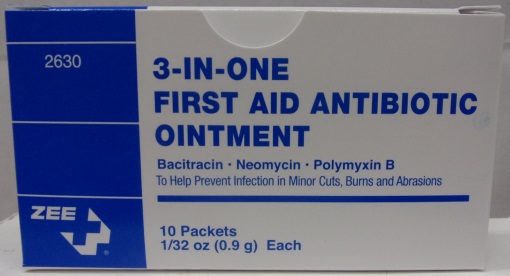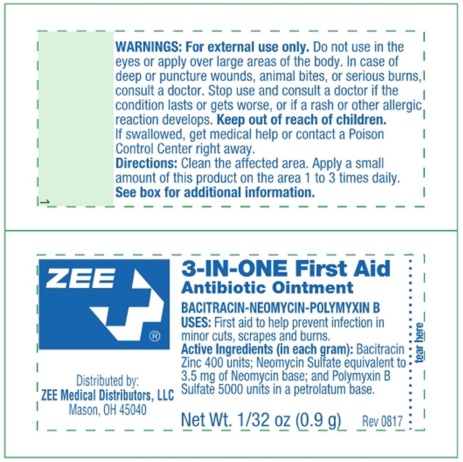 DRUG LABEL: Zee 3-in-One First Aid Antibiotic
NDC: 42961-035 | Form: OINTMENT
Manufacturer: Cintas Corporation
Category: otc | Type: HUMAN OTC DRUG LABEL
Date: 20220712

ACTIVE INGREDIENTS: BACITRACIN ZINC 400 [iU]/100 mg; NEOMYCIN SULFATE 5 mg/100 mg; POLYMYXIN B SULFATE 5000 [iU]/100 mg
INACTIVE INGREDIENTS: PETROLATUM

ZEE 3-in-One First Aid Antibiotic

Active ingredients (in each gram)

Bacitracin zinc 400 units

Neomycin sulfate 5 mg (equivalent to 3.5 mg of neomycin base)

Polymyxin B sulfate 5,000 units

Purpose

First aid antibiotic

First aid antibiotic

First aid antibiotic

Uses

helps prevent infection in minor

- cuts
- burns
- abrasions

Warnings

For external use only.

Allergy Alert: do not use if you are allergic to any of the ingredients

Do not use

- in the eyes
- on large areas of the body

Ask a doctor before use if you have a

- deep or puncture wound
- animal bite
- serious burn

When using this product

do not use longer than one week

Stop use and ask a doctor if

- condition lasts or gets worse
- rash or other allergic reaction develops

Keep out of reach of children.

If swallowed, get medical help or contact a Poison Control Center right away.

Directions

- clean the affected area
- apply a small amount (equal to surface area of tip of finger) on area 1 to 3 times daily
- may be covered with a sterile bandage

Other information

- store at room temperature
- avoid excessive heat above 40°C (104ºF)

Inactive ingredient

petrolatum

Questions?

1-800-327-2704 M-F 8am-5pm

NDC Package Code 42961-035-02 - 10 Count Box

2630
ZEE

3-IN-ONE FIRST AID ANTIBIOTIC OINTMENT

Bacitacin Neomycin Polymyxin B

To Help Prevent Infection in Minor Cuts, Burns and Abrasions

10 Packets 1/32 oz (0.9 g) Each

Distributed by ZEE Medical Distributors, LLC Mason, OH 45040

NDC Package Code 42961-035-01 - Packet

ZEE

Distributed by: ZEE Medical Distributors, LLC Mason, OH 45040

3-IN-ONE First Aid Antibiotic Ointment

Net Wt. 1/32 oz (0.9 g) Rev 0817

tear here